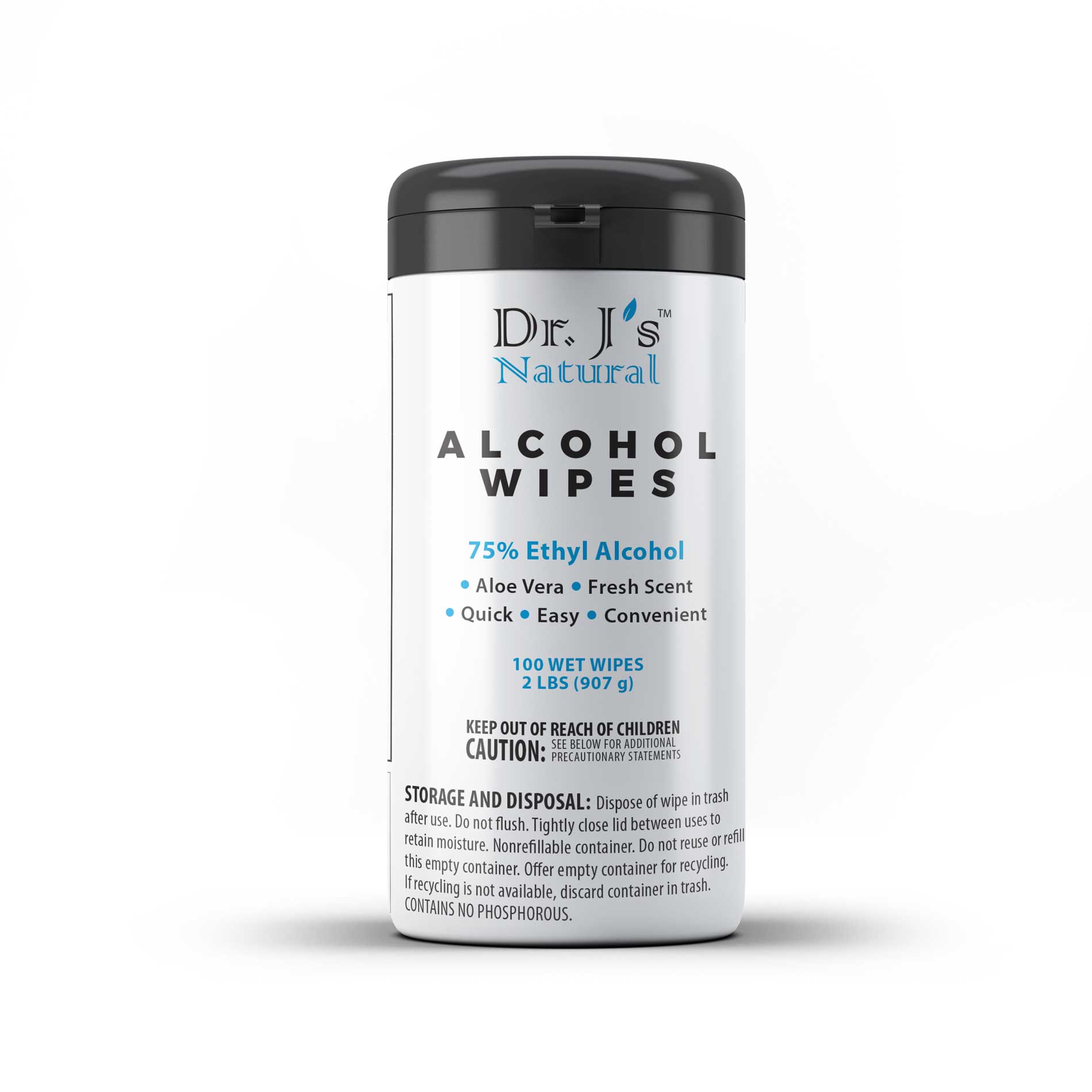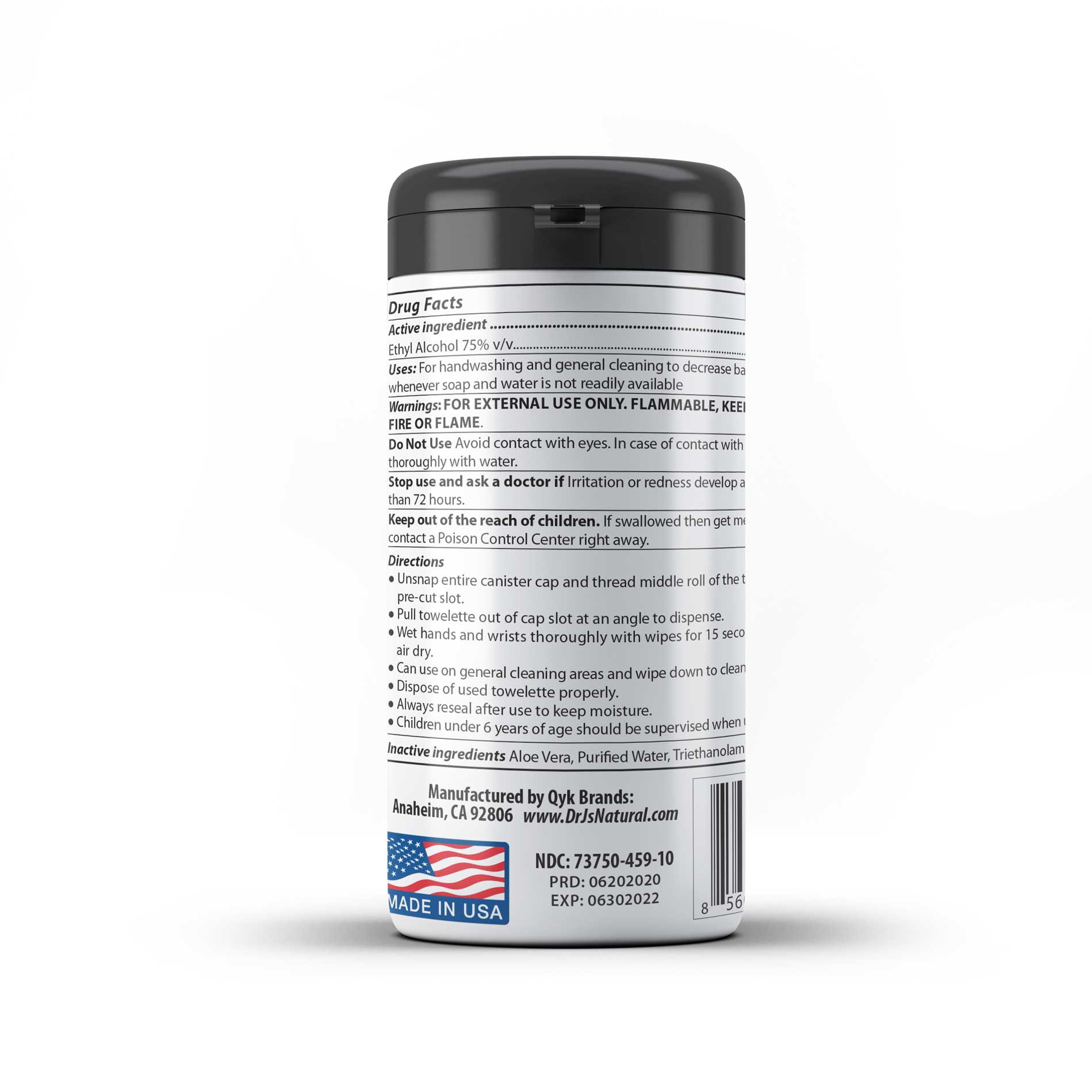 DRUG LABEL: Dr Js Natural 75% Alcohol Wipes
NDC: 73750-459 | Form: CLOTH
Manufacturer: Qyk Brands LLC
Category: otc | Type: HUMAN OTC DRUG LABEL
Date: 20200813

ACTIVE INGREDIENTS: ALCOHOL 75 mL/100 mL
INACTIVE INGREDIENTS: WATER; TRIETHANOLAMINE BENZOATE; LEMON OIL; ALOE VERA LEAF

Drug Facts:

Active ingredient ..................................................................................Purpose
Ethyl Alcohol 75% v/v.............................................................................................Antiseptic

Purpose

Antiseptic

Uses:

Uses: For handwashing and general cleaning to decrease bacteria on skin
whenever soap and water is not readily available

Warnings:

Warnings: FOR EXTERNAL USE ONLY. FLAMMABLE, KEEP AWAY FROM
FIRE OR FLAME.

Do Not Use Avoid contact with eyes. In case of contact with eyes, flush
thoroughly with water.

Stop use:

Stop use and ask a doctor if Irritation or redness develop and persists for more
than 72 hours.

Keep out of the reach of children. If swallowed then get medical help or
contact a Poison Control Center right away.

Directions:

● Unsnap entire canister cap and thread middle roll of the towelette through
pre-cut slot.
● Pull towelette out of cap slot at an angle to dispense.
● Wet hands and wrists thoroughly with wipes for 15 seconds and allow to
air dry.
● Can use on general cleaning areas and wipe down to clean thoroughly.
● Dispose of used towelette properly.
● Always reseal after use to keep moisture.
● Children under 6 years of age should be supervised when using this product.

Inactive ingredients

Inactive ingredients Aloe Vera, Purified Water, Triethanolamine, Essential Oils.

STORAGE AND DISPOSAL: Dispose of wipe in trash
after use. Do not flush. Tightly close lid between uses to
retain moisture. Nonrefillable container. Do not reuse or refill
this empty container. Offer empty container for recycling.
If recycling is not available, discard container in trash.
CONTAINS NO PHOSPHOROUS.

KEEP OUT OF REACH OF CHILDREN
SEE BELOW FOR ADDITIONAL
CAUTION: PRECAUTIONARY STATEMENTS

Package Label: